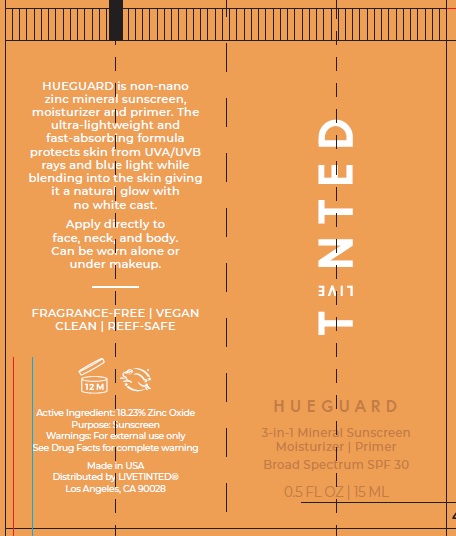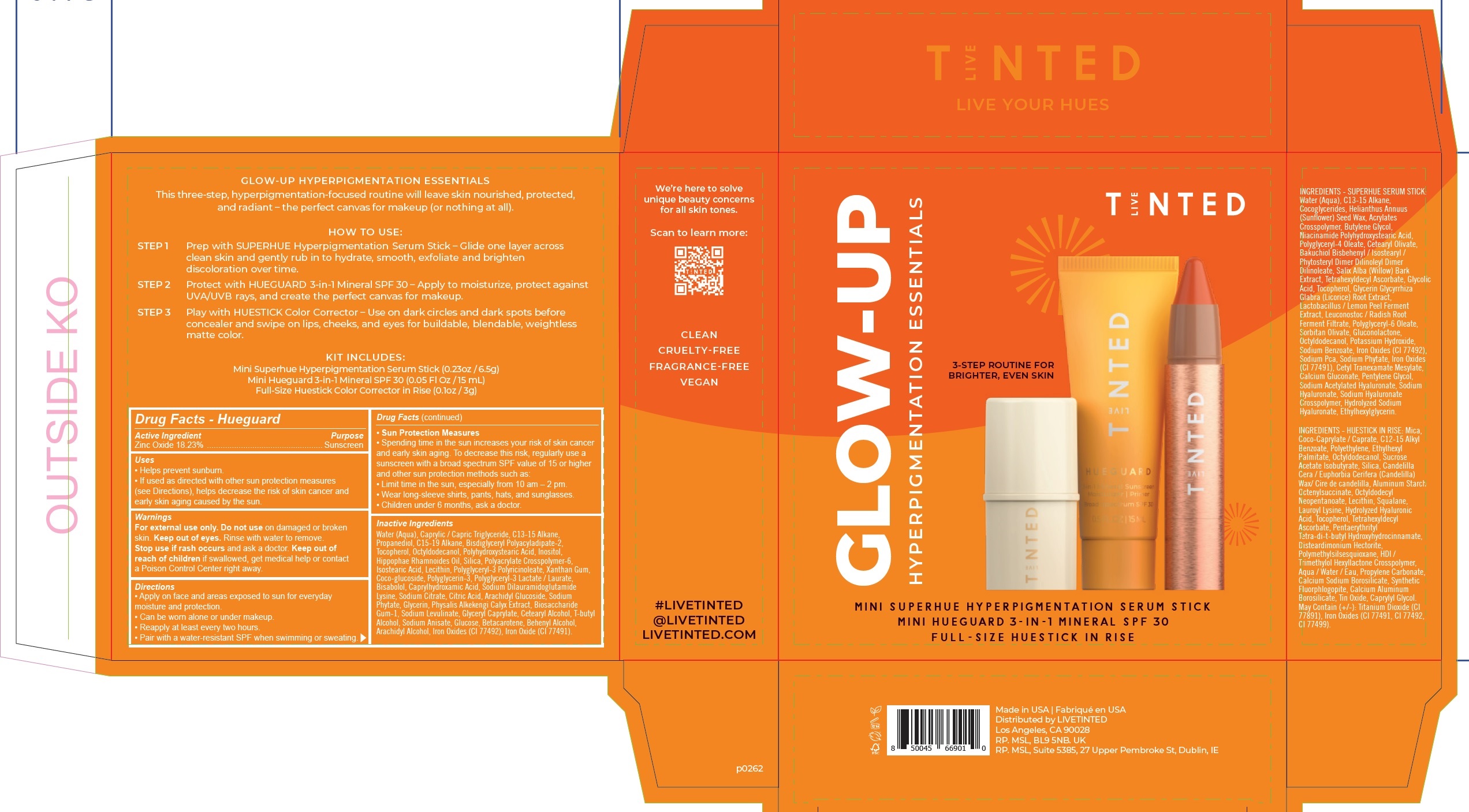 DRUG LABEL: LIVE TINTED Glow-up Hyperpigmentation Essentials
NDC: 82153-280 | Form: KIT | Route: TOPICAL
Manufacturer: Live Tinted, Inc.
Category: otc | Type: HUMAN OTC DRUG LABEL
Date: 20231028

ACTIVE INGREDIENTS: ZINC OXIDE 182.3 mg/1 mL
INACTIVE INGREDIENTS: WATER; MEDIUM-CHAIN TRIGLYCERIDES; C13-15 ALKANE; PROPANEDIOL; C15-19 ALKANE; TOCOPHEROL; OCTYLDODECANOL; INOSITOL; SILICON DIOXIDE; AMMONIUM ACRYLOYLDIMETHYLTAURATE, DIMETHYLACRYLAMIDE, LAURYL METHACRYLATE AND LAURETH-4 METHACRYLATE COPOLYMER, TRIMETHYLOLPROPANE TRIACRYLATE CROSSLINKED (45000 MPA.S); ISOSTEARIC ACID; XANTHAN GUM; COCO GLUCOSIDE; POLYGLYCERIN-3; LEVOMENOL; CAPRYLHYDROXAMIC ACID; SODIUM DILAURAMIDOGLUTAMIDE LYSINE; SODIUM CITRATE, UNSPECIFIED FORM; CITRIC ACID MONOHYDRATE; ARACHIDYL GLUCOSIDE; PHYTATE SODIUM; GLYCERIN; ALKEKENGI OFFICINARUM CALYX; BIOSACCHARIDE GUM-1; SODIUM LEVULINATE; GLYCERYL CAPRYLATE; CETOSTEARYL ALCOHOL; TERT-BUTYL ALCOHOL; SODIUM ANISATE; ANHYDROUS DEXTROSE; BETA CAROTENE; DOCOSANOL; ARACHIDYL ALCOHOL; FERRIC OXIDE YELLOW; FERRIC OXIDE RED

LIVE TINTED. Glow-up Hyperpigmentation Essentials

Active Ingredient

Zinc Oxide 18.23%

Purpose

Sunscreen

Uses

• Helps prevent sunburn. • If used as directed with other sun protection measures (see Directions), helps decrease the risk of skin cancer and early skin aging caused by the sun.

Warnings

For external use only

Do not use

on damaged or broken skin. Keep out of eyes. Rinse with water to remove.

Stop use

if rash occurs and ask a doctor.

Keep out of reach of children

if swallowed, get medical help orcontact a Poison Control Center right away.

Directions

• Apply liberally to face and neck for everyday moisture and protection. • Can be worn alone or under makeup. • Reapply at least every two hours. • Pair with a waterresistant SPF when swimming or sweating.

Sun Protection Measures • Spending time in the sun increases your risk of skin cancer and early skin aging. To decrease this risk, regularly use a sunscreen with a broad spectrum SPF value of 15 or higher and other sun protection methods such as: • Limit time in the sun, especially from 10 a.m. – 2 p.m. • Wear long-sleeve shirts, pants, hats, and sunglasses. • Children under 6 months, ask a doctor.

Inactive Ingredient

Water (Aqua), Caprylic Capric Triglyceride, C13-15 Alkane, Propanediol, C15-19 Alkane, Bisdiglyceryl Polyacyladipate-2, Tocopherol, Octyldodecanol, Polyhydroxystearic Acid, Inositol, Hippophae Rhamnoides Oil, Silica, Polyacrylate Cross-Polymer-6, Isostearic Acid, Lecithin, Polyglyceryl- 3 Polyricinoleate, Xanthan Gum, Cocoglucoside, Polyglycerin-3, Polyglyceryl-3 Lactate / Laurate, Bisabolol, Caprylhydroxamic Acid, Sodium Dilauramidoglutamide Lysine, Sodium Citrate, Citric Acid, Arachidyl Glucoside, Sodium Phytate, Glycerin, Physalis Alkekengi Calyx Extract, Biosaccharide Gum-1, Sodium Levulinate, Glyceryl Caprylate, Cetearyl Alcohol, T-butyl Alcohol, Sodium Anisate, Glucose, Betacarotene, Behenyl Alcohol, Arachidyl Alcohol, Iron Oxides (CI 77492, CI 77491)